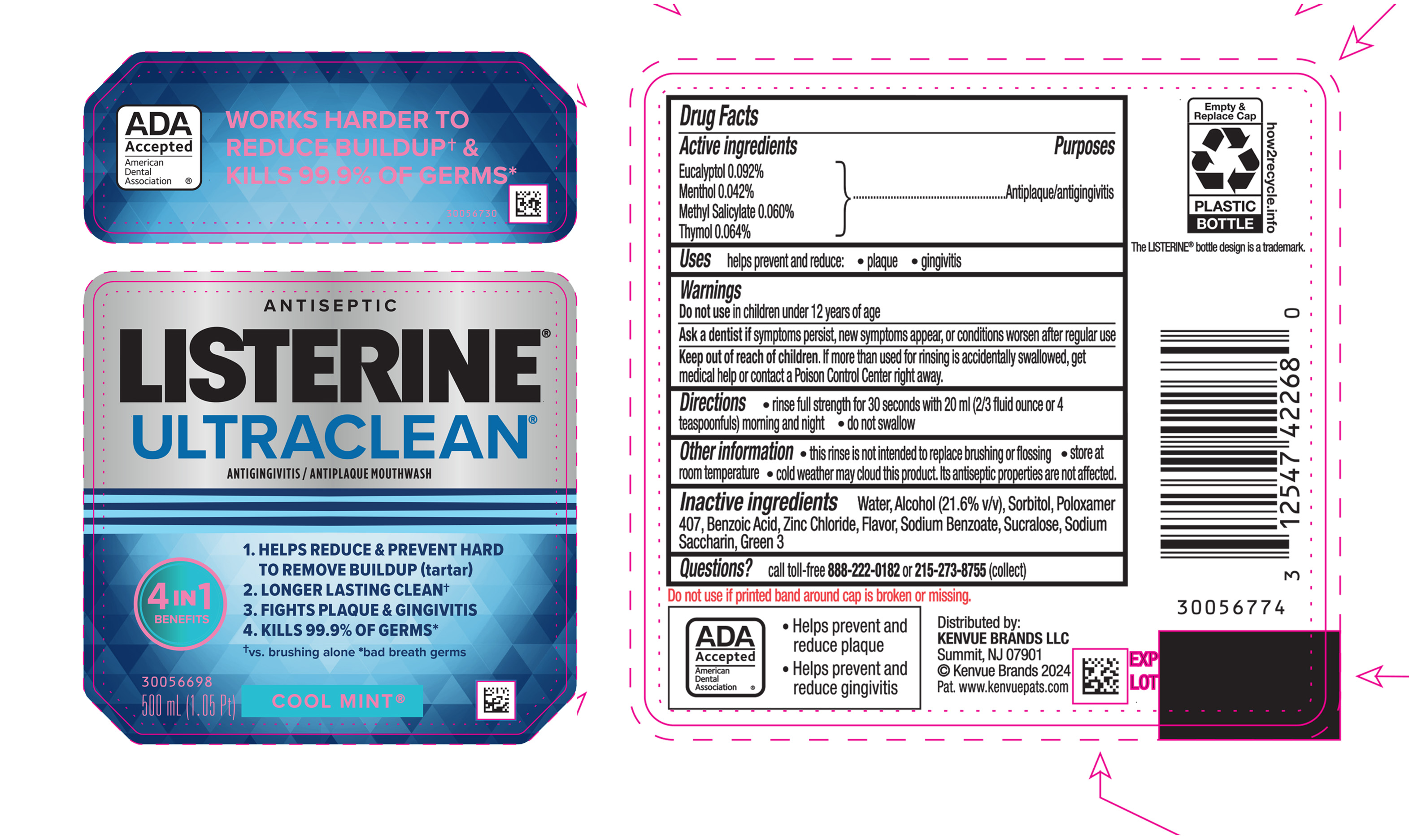 DRUG LABEL: Listerine Ultraclean Antiseptic
NDC: 69968-0788 | Form: MOUTHWASH
Manufacturer: Kenvue Brands LLC
Category: otc | Type: HUMAN OTC DRUG LABEL
Date: 20250410

ACTIVE INGREDIENTS: THYMOL 0.64 mg/1 mL; EUCALYPTOL 0.92 mg/1 mL; MENTHOL, UNSPECIFIED FORM 0.42 mg/1 mL; METHYL SALICYLATE 0.6 mg/1 mL
INACTIVE INGREDIENTS: WATER; ALCOHOL; SORBITOL; POLOXAMER 407; BENZOIC ACID; ZINC CHLORIDE; SODIUM BENZOATE; SUCRALOSE; SACCHARIN SODIUM; FD&C GREEN NO. 3

Listerine Ultraclean Antiseptic Cool Mint

Drug Facts

ACTIVE INGREDIENT

PURPOSE

Active ingredients | Purposes
Eucalyptol (0.092%) | Antiplaque/antigingivitis
Menthol (0.042%) | Antiplaque/antigingivitis
Methyl Salicylate (0.060%) | Antiplaque/antigingivitis
Thymol (0.064%) | Antiplaque/antigingivitis

Uses

helps prevent and reduce:

- plaque
- gingivitis

Warnings

Do not use in children under 12 years of age

ASK DOCTOR/PHARMACIST

Ask a dentist if symptoms persist, new symptoms appear, or conditions worsen after regular use

Keep out of reach of children. If more than used for rinsing is accidentally swallowed, get medical help or contact a Poison Control Center right away.

Directions

• rinse full strength for 30 seconds with 20 mL (2/3 fluid ounce or 4 teaspoonfuls) morning and night

• do not swallow

Other information

- this rinse is not intended to replace brushing or flossing
- store at room temperature
- cold weather may cloud this product. Its antiseptic properties are not affected.

Inactive ingredients

Water, Alcohol (21.6% v/v), Sorbitol, Poloxamer 407, Benzoic Acid, Zinc Chloride, Flavor, Sodium Benzoate, Sucralose, Sodium Saccharin, Green 3

Questions?

call toll-free 888-222-0182 or 215-273-8755 (collect)

Distributed by:
KENVUE BRANDS LLC
Summit, NJ 07901

PRINCIPAL DISPLAY PANEL - 500 mL Bottle Label

ANTISEPTIC

LISTERINE®

ULTRACLEAN®

ANTIGINGIVITIS / ANTIPLAQUE MOUTHWASH

4 IN 1

BENEFITS

1. HELPS REDUCE & PREVENT HARD

TO REMOVE BUILDUP (tartar)

2. LONGER LASTING CLEAN†
3. FIGHTS PLAQUE & GINGIVITIS
4. KILLS 99.9% OF GERMS*

†vs. brushing alone*bad breath germs

COOL MINT®

500 mL (1.05 Pt)